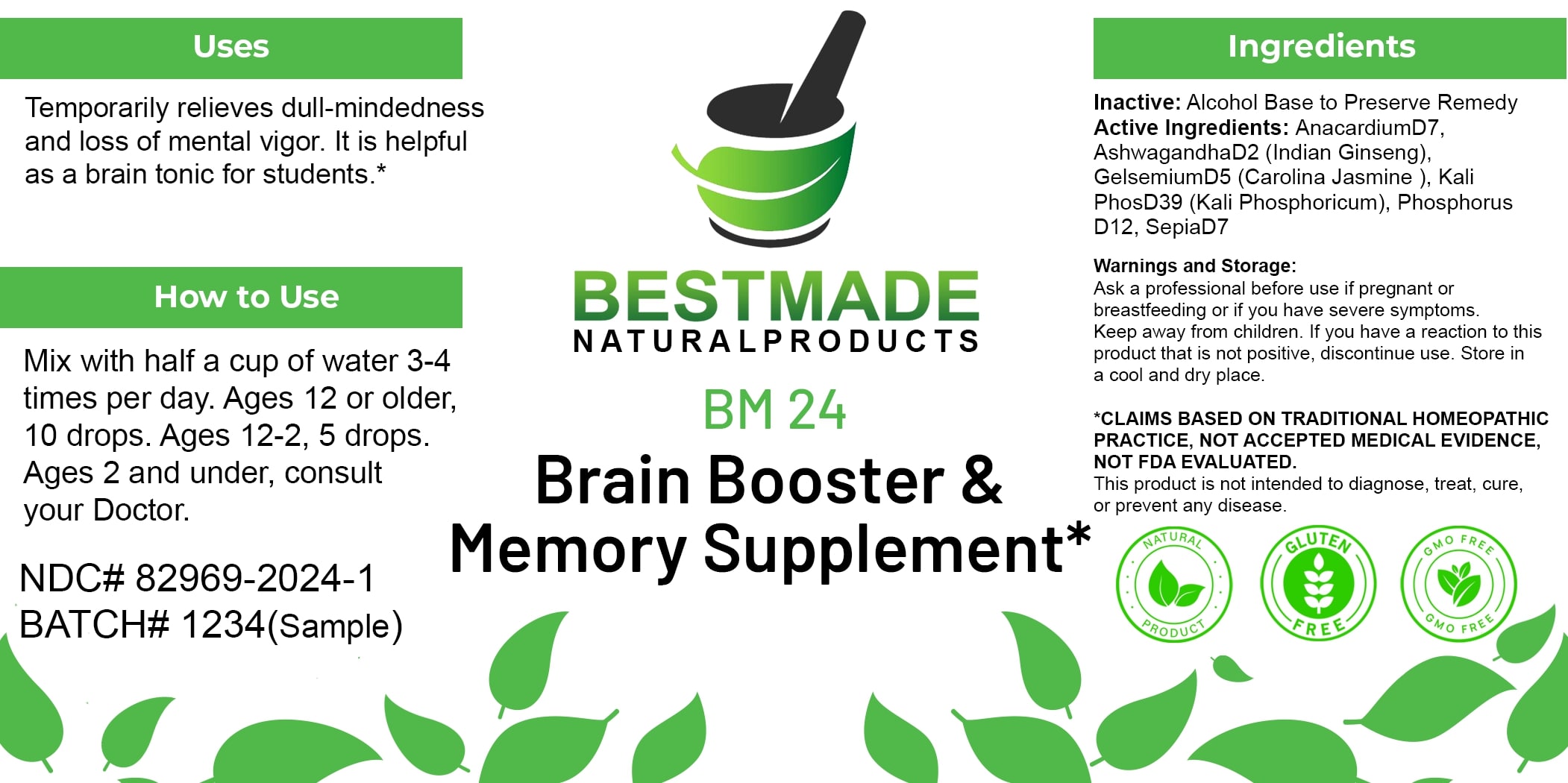 DRUG LABEL: Bestmade Natural Products BM24
NDC: 82969-2024 | Form: LIQUID
Manufacturer: Bestmade Natural Products
Category: homeopathic | Type: HUMAN OTC DRUG LABEL
Date: 20250123

ACTIVE INGREDIENTS: GELSEMIUM SEMPERVIRENS ROOT 30 [hp_C]/30 [hp_C]; POTASSIUM PHOSPHATE, UNSPECIFIED FORM 30 [hp_C]/30 [hp_C]; PHOSPHORUS 30 [hp_C]/30 [hp_C]; SEPIA OFFICINALIS JUICE 30 [hp_C]/30 [hp_C]; WITHANIA SOMNIFERA WHOLE 30 [hp_C]/30 [hp_C]; SEMECARPUS ANACARDIUM JUICE 30 [hp_C]/30 [hp_C]; ATROPA BELLADONNA 30 [hp_C]/30 [hp_C]
INACTIVE INGREDIENTS: ALCOHOL 30 [hp_C]/30 [hp_C]

BM24

DOSAGE AND ADMINISTRATION

How to Use

Mix with half a cup of water 3-4 times per day. Ages 12 or older, 10 drops. Ages 12-2, 5 drops. Ages 2 and under, consult your Doctor.

INACTIVE INGREDIENT

Ingredients

Inactive: Alcohol Base to Preserve Remedy

Uses

Temporarily relieves dull-mindedness and loss of mental vigor. It is helpful as a brain tonic for students.*

*CLAIMS BASED ON TRADITIONAL HOMEOPATHIC PRACTICE, NOT ACCEPTED MEDICAL EVIDENCE, NOT FDA EVALUATED.

This product is not intended to diagnose, treat, cure, or prevent any disease.

Uses

Temporarily relieves dull-mindedness and loss of mental vigor. It is helpful as a brain tonic for students.*

*CLAIMS BASED ON TRADITIONAL HOMEOPATHIC PRACTICE, NOT ACCEPTED MEDICAL EVIDENCE, NOT FDA EVALUATED.

This product is not intended to diagnose, treat, cure, or prevent any disease.

Active Ingredients:

AnacardiumD7, AshwagandhaD2 (Indian Ginseng), GelsemiumD5 (Carolina Jasmine), Kali PhosD39 (Kali Phosphoricum), Phosphorus D12, SepiaD7

KEEP OUT OF REACH OF CHILDREN

Warnings and Storage:

Ask a professional before use if pregnant or breastfeeding or if you have severe symptoms. Keep away from children. If you have a reaction to this product that is not positive, discontinue use. Store in a cool and dry place.

Warnings and Storage:

Ask a professional before use if pregnant or breastfeeding or if you have severe symptoms. Keep away from children. If you have a reaction to this product that is not positive, discontinue use. Store in a cool and dry place.

*CLAIMS BASED ON TRADITIONAL HOMEOPATHIC PRACTICE, NOT ACCEPTED MEDICAL EVIDENCE, NOT FDA EVALUATED.

This product is not intended to diagnose, treat, cure, or prevent any disease.

Entire package label